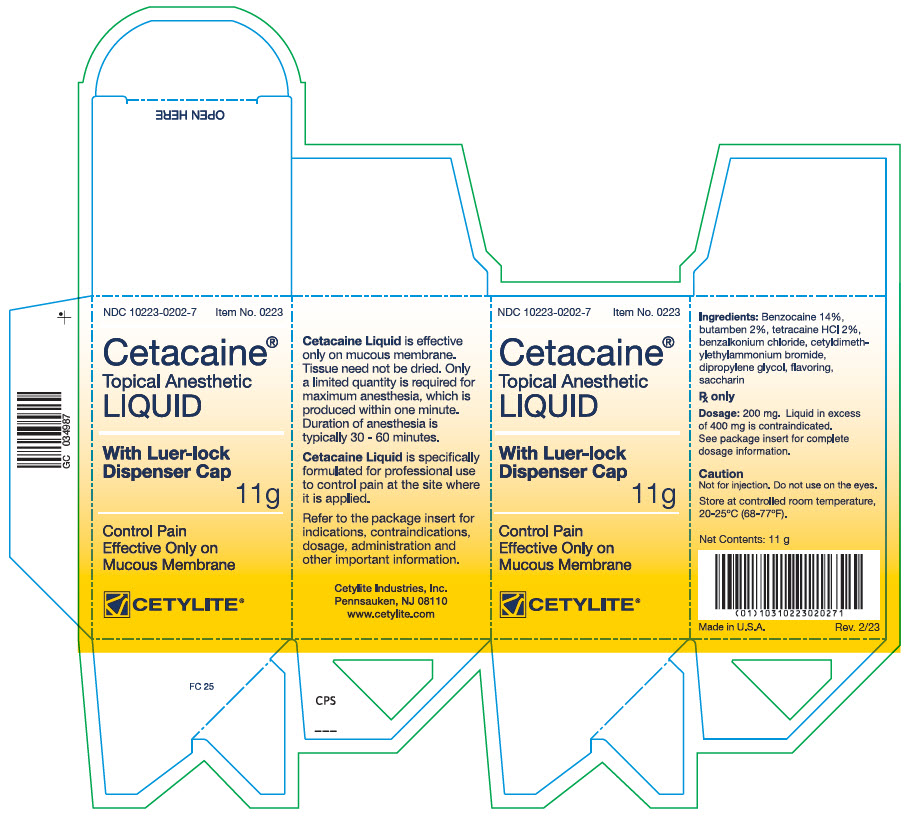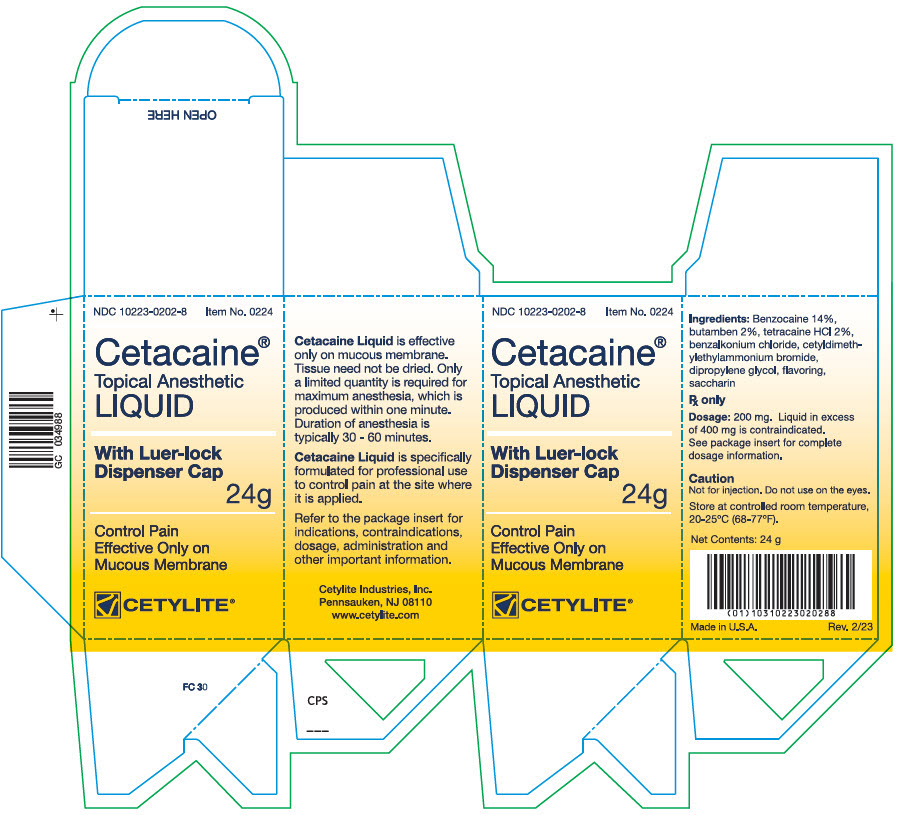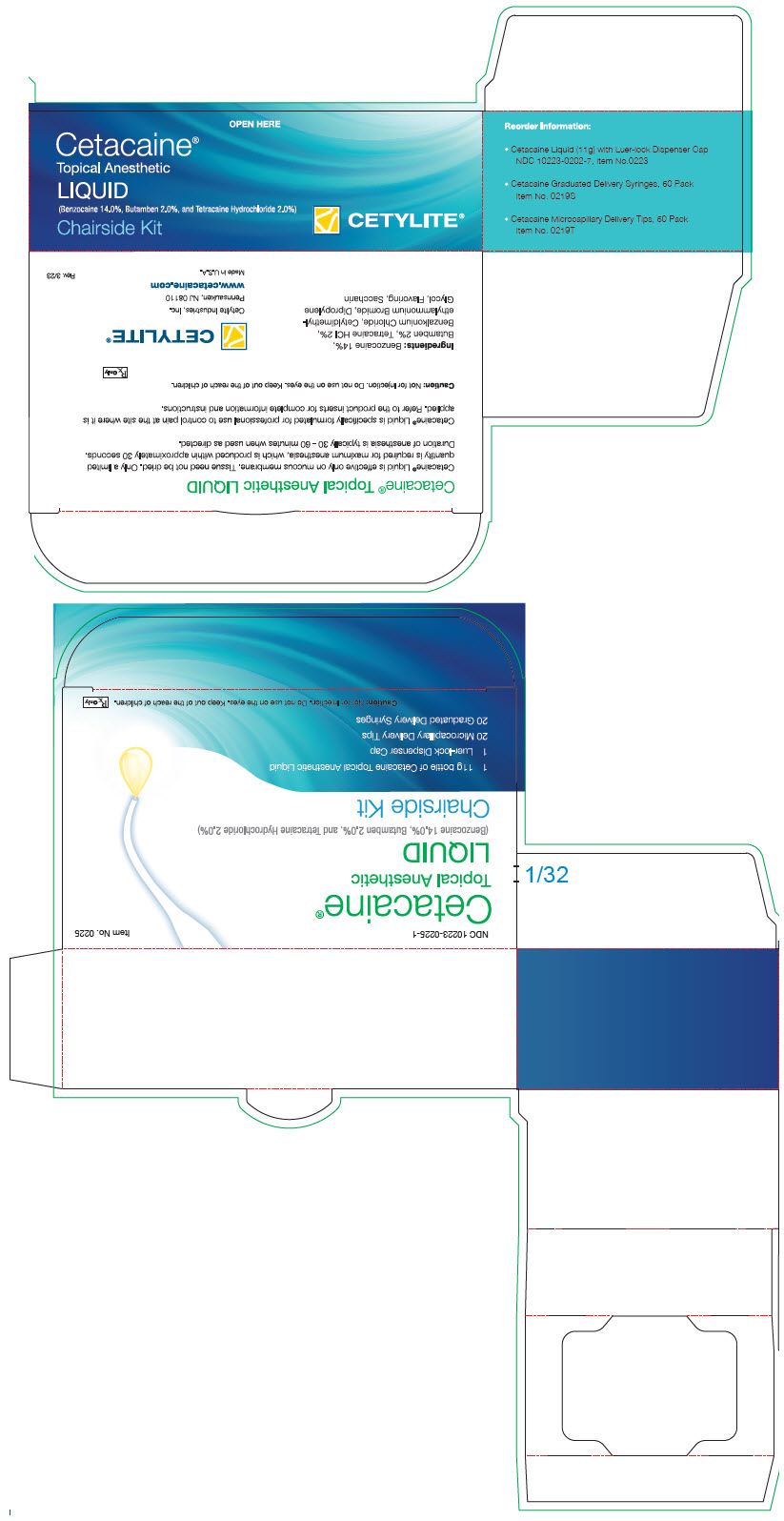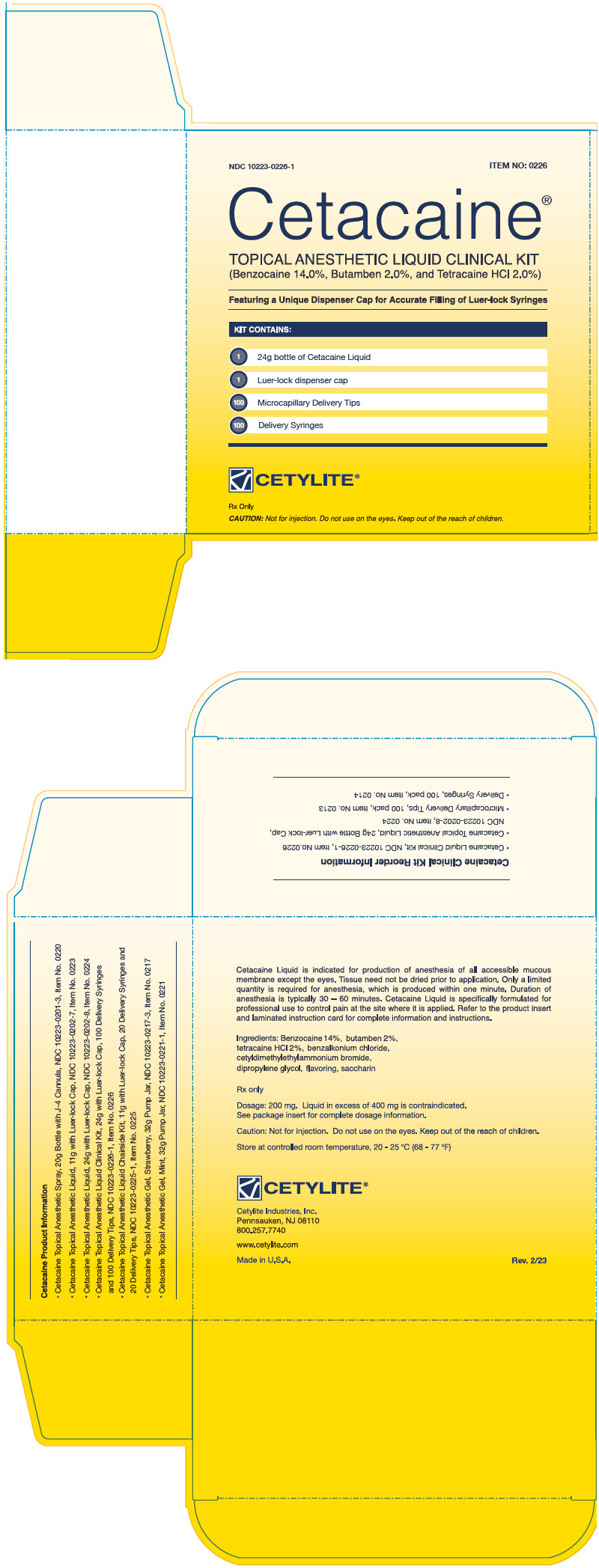 DRUG LABEL: Cetacaine Anesthetic
NDC: 10223-0202 | Form: SOLUTION
Manufacturer: Cetylite Industries, Inc.
Category: prescription | Type: HUMAN PRESCRIPTION DRUG LABEL
Date: 20250110

ACTIVE INGREDIENTS: Benzocaine 0.028 g/0.2 g; Butamben 0.004 g/0.2 g; Tetracaine Hydrochloride 0.004 g/0.2 g
INACTIVE INGREDIENTS: Dipropylene glycol; Saccharin; Benzalkonium chloride; Mecetronium Bromide

Cetacaine
Topical Anesthetic
Spray and Liquid

Active ingredients
Benzocaine | 14.0%
Butamben | 2.0%
Tetracaine Hydrochloride | 2.0%
Contains
Benzalkonium Chloride | 0.5%
Cetyl Dimethyl Ethyl Ammonium Bromide | 0.005%
In a bland, water-soluble base.

Rx Only.

STORAGE AND HANDLING

Store at controlled room temperature 20-25°C (68-77°F)

Action

The onset of Cetacaine-produced anesthesia is rapid (approximately 30 seconds) and the duration of anesthesia is typically 30-60 minutes, when used as directed. This effect is due to the rapid onset, but short duration of action of Benzocaine coupled with the slow onset, but extended duration of Tetracaine HCI and bridged by the intermediate action of Butamben.

These agents act by reversibly blocking nerve conduction. Speed and duration of action is determined by the ability of the agent to be absorbed by the mucous membrane and nerve sheath and then to diffuse out, and ultimately be metabolized (primarily by plasma cholinesterases) to inert metabolites which are excreted in the urine.

Indications

Cetacaine is a topical anesthetic indicated for the production of anesthesia of all accessible mucous membrane except the eyes. Cetacaine Spray is indicated for use to control pain or gagging.

Cetacaine in all forms is indicated to control pain and for use for surgical or endoscopic or other procedures in the ear, nose, mouth, pharynx, larynx, trachea, bronchi, and esophagus. It may also be used for vaginal or rectal procedures when feasible.

Dosage and Administration

Cetacaine Spray should be applied for approximately one second or less for normal anesthesia. Only a limited quantity of Cetacaine is required for anesthesia. Spray in excess of two seconds is contraindicated. Each one-second spray contains an average of 200 mg of product, not including propellant.

To apply, insert the cannula firmly onto the protruding plastic stem on the bottle and press the cannula forward to actuate the spray valve. The cannula may be removed and reinserted as many times as required for cleaning, or sterilization, and is autoclavable.

Cetacaine Liquid

Apply 200 mg liquid (approximately 0.2 mL) directly to tissue. Liquid in excess of 400 mg (approximately 0.4 mL) is contraindicated.

To apply, remove and discard the shipping cap from the bottle. Replace it with the supplied Luer-lock cap. Caution: Do not over-tighten. Remove small cap from luer-lock port, retaining it for replacement after use. Port allows for a single dip of a cotton or brush applicator for application directly to accessible mucous membrane. For application into periodontal pockets, Cetylite Luer-lock syringes and Microcapillary Delivery Tips are recommended. Cetylite Syringes are clearly marked in (4) 0.1 mL increments. To fill, attach syringe to port by gently twisting clockwise until secure. Invert and draw desired amount of liquid into the syringe. Remove filled syringe and attach Microcapillary Delivery Tip to the syringe. Tip may be bent to improve access. Apply drop-wise to accessible mucous membrane (such as buccal and lingual sulcus) by slowly depressing the syringe plunger. Discard all applicators after use.

An appropriate pediatric dosage has not been established for Cetacaine Spray or Cetacaine Liquid.

Dosages should be reduced in the debilitated elderly, acutely ill, and very young patients (i.e., children 2 years and older).

Do not use Cetacaine Spray or Cetacaine Liquid to treat infants or children younger than 2 years.

Tissue need not be dried prior to application of Cetacaine. Cetacaine should be applied directly to the site where pain control is required. Anesthesia is produced within one minute with an approximate duration of thirty minutes. Each 200 mg dose of Cetacaine (Spray or Liquid) contains 28 mg of benzocaine, 4 mg of butamben and 4 mg of tetracaine HCl.

WARNINGS AND PRECAUTIONS

Methemoglobinemia

Cases of methemoglobinemia have been reported in association with local anesthetic use. Although all patients are at risk for methemoglobinemia, patients with glucose-6-phosphate dehydrogenase deficiency, congenital or idiopathic methemoglobinemia, cardiac or pulmonary compromise, infants under 6 months of age, and concurrent exposure to oxidizing agents or their metabolites are more susceptible to developing clinical manifestations of the condition. If local anesthetics must be used in these patients, close monitoring for symptoms and signs of methemoglobinemia is recommended.

Signs and symptoms of methemoglobinemia may occur immediately or may be delayed some hours after exposure and are characterized by a cyanotic skin discoloration and abnormal coloration of the blood. Methemoglobin levels may continue to rise; therefore, immediate treatment is required to avert more serious central nervous system and cardiovascular adverse effects, including seizures, coma, arrhythmias, and death. Discontinue Cetacaine and any other oxidizing agents. Depending on the severity of the symptoms, patients may respond to supportive care, i.e., oxygen therapy, hydration. More severe symptoms may require treatment with methylene blue, exchange transfusion, or hyperbaric oxygen.

DRUG INTERACTIONS

Patients that are administered local anesthetics may be at increased risk of developing methemoglobinemia when concurrently exposed to the following oxidizing agents:

Class | Examples
Nitrates/Nitrites | nitroglycerin, nitroprusside, nitric oxide, nitrous oxide
Local anesthetics | benzocaine, lidocaine, bupivacaine, mepivacaine, tetracaine, prilocaine, procaine, articaine, ropivacaine
Antineoplastic agents | cyclophosphamide, flutamide, rasburicase, ifosfamide, hydroxyurea
Antibiotics | dapsone, sulfonamides, nitrofurantoin, para-aminosalicylic acid
Antimalarials | chloroquine, primaquine
Anticonvulsants | phenytoin, sodium valproate, phenobarbital
Other drugs | acetaminophen, metoclopramide, sulfa drugs (i.e., sulfasalazine), quinine

PATIENT COUNSELING INFORMATION

Inform patients that use of local anesthetics may cause methemoglobinemia, a serious condition that must be treated promptly. Advise patients or caregivers to stop use and seek immediate medical attention if they or someone in their care experience the following signs or symptoms: pale, gray, or blue colored skin (cyanosis); headache; rapid heart rate; shortness of breath; lightheadedness; or fatigue.

Hypersensitivity Reactions

Unpredictable adverse reactions (i.e. hypersensitivity, including anaphylaxis) are extremely rare.

Localized allergic reactions may occur after prolonged or repeated use of any aminobenzoate anesthetic. The most common adverse reaction caused by local anesthetics is contact dermatitis characterized by erythema and pruritus that may progress to vesiculation and oozing. This occurs most commonly in patients following prolonged self-medication, which is contraindicated. If rash, urticaria, edema, or other manifestations of allergy develop during use, the drug should be discontinued. To minimize the possibility of a serious allergic reaction, Cetacaine preparations should not be applied for prolonged periods except under continual supervision. Dehydration of the epithelium or an escharotic effect may also result from prolonged contact.

Use in Pregnancy

Safe use of Cetacaine has not been established with respect to possible adverse effects upon fetal development. Therefore, Cetacaine should not be used during early pregnancy, unless in the judgement of a physician, the potential benefits outweigh the unknown hazards. Routine precaution for the use of any topical anesthetic should be observed when Cetacaine is used.

Contraindications

Do not use Cetacaine Spray or Cetacaine Liquid to treat infants or children younger than 2 years.

Cetacaine is not suitable and should never be used for injection. Do not use on the eyes. To avoid excessive systemic absorption, Cetacaine should not be applied to large areas of denuded or inflamed tissue. Cetacaine should not be administered to patients who are hypersensitive to any of its ingredients or to patients known to have cholinesterase deficiencies. Tolerance may vary with the status of the patient.

Cetacaine should not be used under dentures or cotton rolls, as retention of the active ingredients under a denture or cotton roll could possibly cause an escharotic effect. Routine precaution for the use of any topical anesthetic should be observed when using Cetacaine.

Autoclavable Cannula for Cetacaine Spray

- The supplied 4" stainless steel cannula for Cetacaine Spray is specially designed for accessibility and application of Cetacaine, at the required site of pain control. Replacement cannulas are available as a 10-pack (Item # 0205).

Luer-lock Syringes and Microcapillary Delivery Tips for Cetacaine Liquid

- Cetacaine Liquid Syringes and Microcapillary Delivery Tips are supplied with the Cetacaine Liquid Chairside Kit (Item # 0218) and Clinical Kit (Item # 0212). They also can be purchased separately. Syringes are available in packs of 50 (Item # 0219S) or packs of 100 (Item # 0214). Delivery Tips are available in packs of 50 (Item # 0219T) or packs of 100 (Item # 0213).

How Supplied

- Cetacaine Spray, 20 g bottle, including propellant [WARNING Cetacaine Spray contains CFC-114 and CFC-11, substances which harm public health and environment by destroying ozone in the upper atmosphere. The propellant leak rate of Cetacaine Spray does not meet the USP requirements.] (Item # 0220, NDC 10223-0201-3) which includes one cannula.
- Cetacaine Spray Single Patient Use, 5 g bottle, including propellant (Item # 0222, NDC 10223-0201-4) which includes one cannula.
- Cetacaine Liquid Chairside Kit (Item # 0218 NDC 10223-0202-6) which includes one 14 g bottle of Cetacaine Liquid with Luer-lock dispenser cap, 20 syringes and 20 delivery tips.
- Cetacaine Liquid Clinical Kit (Item # 0212, NDC 10223-0202-5) which includes one 30 g bottle of Cetacaine Liquid with Luer-lock dispenser cap, 100 syringes and 100 delivery tips.
- Cetacaine Liquid, 14 g bottle (Item # 0203, NDC 10223-0202-2) with Luer-lock dispenser cap.
- Cetacaine Liquid, 30 g bottle (Item # 0211, NDC 10223-0202-4) with Luer-lock dispenser cap.

Made in USA

Cetylite Industries, Inc.
Pennsauken, NJ 08110

Rev. 10 /18

www.cetylite.com

PRINCIPAL DISPLAY PANEL - 11 g Bottle Box

NDC 10223-0202-7
Item No. 0223

Cetacaine®
Topical Anesthetic
LIQUID

With Luer-lock
Dispenser Cap

11g

Control Pain
Effective Only on
Mucous Membrane

CETYLITE®

PRINCIPAL DISPLAY PANEL - 24 g Bottle Box

NDC 10223-0202-8
Item No. 0224

Cetacaine®
Topical Anesthetic
LIQUID

With Luer-lock
Dispenser Cap

24g

Control Pain
Effective Only on
Mucous Membrane

CETYLITE®

PRINCIPAL DISPLAY PANEL - 11 g Bottle Kit

OPEN HERE

Cetacaine®

Topical Anesthetic

LIQUID

(Benzocaine 14.0%, Butamben 2.0%, and Tetracaine Hydrochloride 2.0%)

Chairside Kit

CETYLITE®

PRINCIPAL DISPLAY PANEL - 24 g Bottle Kit

NDC 10223-0226-1
ITEM NO: 0226

Cetacaine®
TOPICAL ANESTHETIC LIQUID CLINICAL KIT
(Benzocaine 14.0%, Butamben 2.0%, and Tetracaine HCl 2.0%)

Featuring a Unique Dispenser Cap for Accurate Filling of Luer-lock Syringes

KIT CONTAINS:

1 24g bottle of Cetacaine Liquid

1 Luer-lock dispenser cap

100 Microcapillary Delivery Tips

100 Delivery Syringes

CETYLITE®

Rx Only

CAUTION: Not for injection. Do not use on the eyes. Keep out of reach of children.